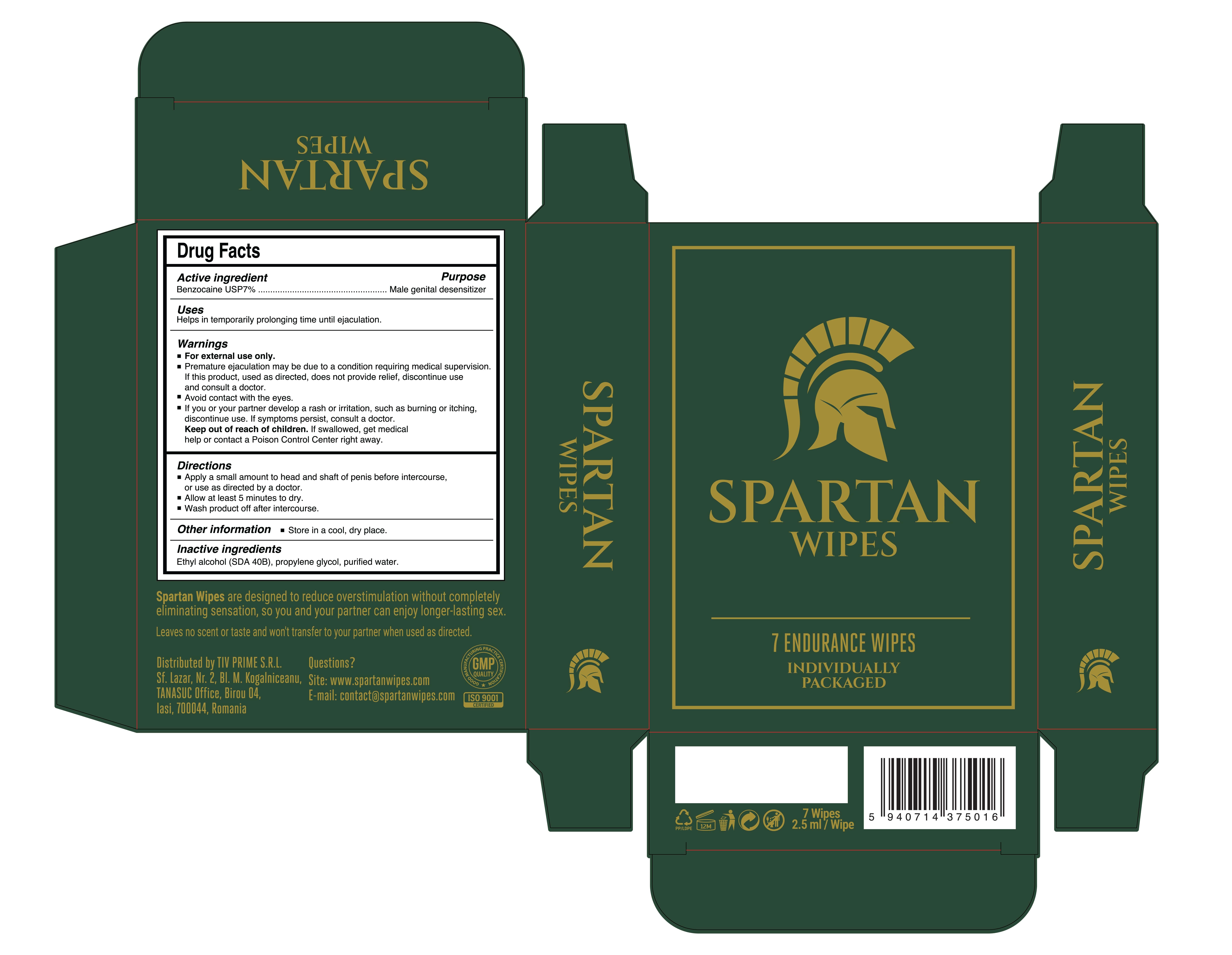 DRUG LABEL: SPARTAN WIPES
NDC: 84930-111 | Form: CLOTH
Manufacturer: TIV PRIME SRL
Category: otc | Type: HUMAN OTC DRUG LABEL
Date: 20251218

ACTIVE INGREDIENTS: BENZOCAINE 7 mg/100 mL
INACTIVE INGREDIENTS: PROPYLENE GLYCOL; ALCOHOL; WATER

Brand Owner SPARTAN WIPES

Active Ingredient(s)

Benzocaine USP 7% Male Genital Desensitizer

Purpose

Male Genital Desensitizer

Use

Helps in temporarily prolonging time until ejaculation.

Warnings

For external use only.

Do not use if you or your partner are allergic to benzocaine.

When using this product, avoid contact with the eyes.

Before using the wipe on a regular basis, apply a small amount to your forearm. If an allergic reaction occurs, discontinue use.

STOP USE

Premature ejaculation may be due to a condition requiring medical
supervision.

You or your partner develop a rash or irritation, such as burning or itching.

Keep out of reach of children. If swallowed, get medical help or contact a Poison Control Center right away.

Directions

Apply a small amount to head and shaft of penis before intercourse.
Allow at least 5 minutes to dry.

Inactive ingredients

Ethyl alcohol (SDA 408), propylene glycol, purified water.

OTHER SAFETY INFORMATION

Store in a cool, dry place.